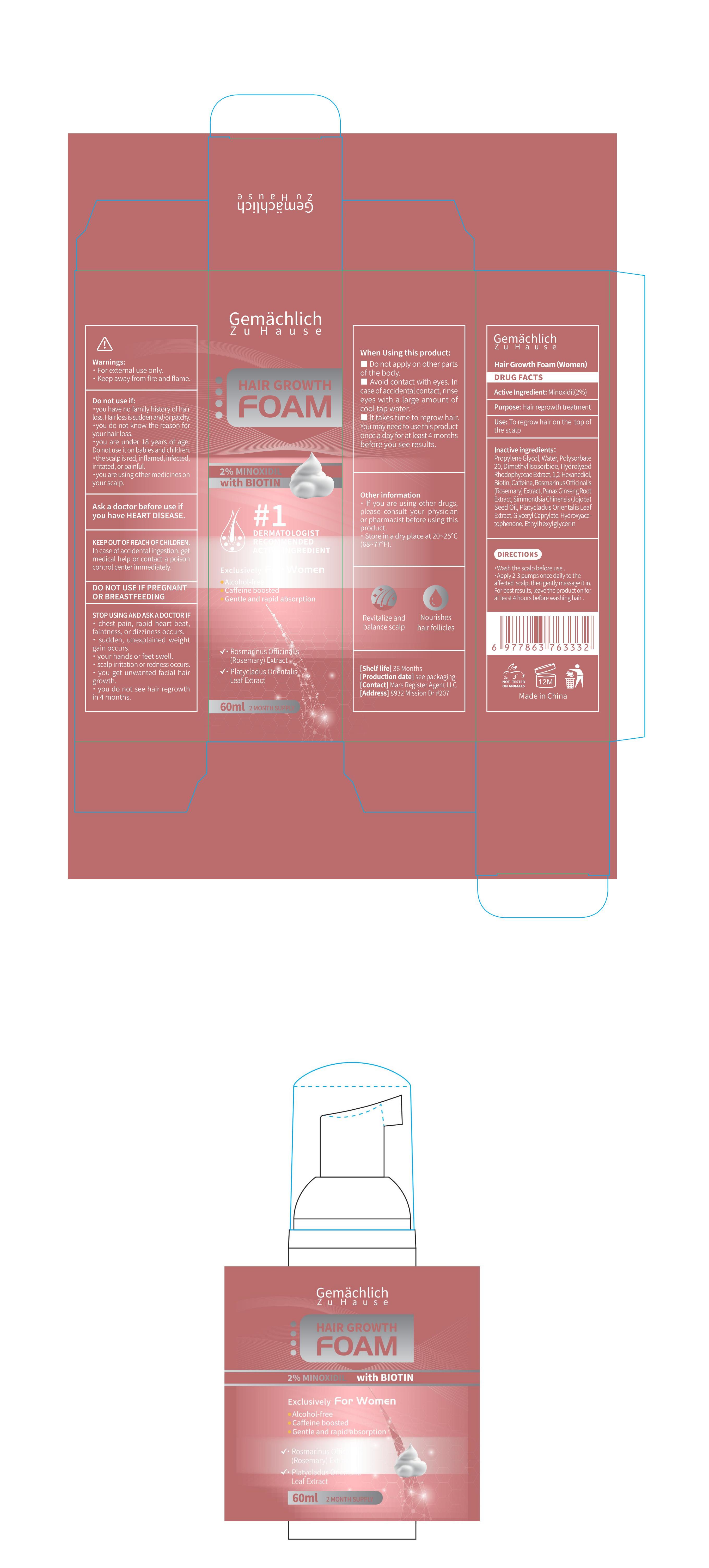 DRUG LABEL: Gemachlich ZuHause Hair Growth Foam (Women)
NDC: 76986-009 | Form: LIQUID
Manufacturer: Guangdong Quadrant Ecological Technology Co., Ltd.
Category: otc | Type: HUMAN OTC DRUG LABEL
Date: 20250727

ACTIVE INGREDIENTS: MINOXIDIL 2 g/100 mL
INACTIVE INGREDIENTS: POLYSORBATE 20; GLYCERYL CAPRYLATE; 2'-HYDROXYACETOPHENONE; PLATYCLADUS ORIENTALIS LEAF; ETHYLHEXYLGLYCERIN; BIOTIN; ROSMARINUS OFFICINALIS (ROSEMARY) LEAF OIL; SKYRIN; PANAX GINSENG ROOT; SIMMONDSIA CHINENSIS (JOJOBA) SEED OIL; PROPYLENE GLYCOL; 1,2-HEXANEDIOL; WATER; DIMETHYL ISOSORBIDE; CAFFEINE

76986-009

Active Ingredient

Minoxidil 2%

Purpose

Hair regrowth treatment

Use

To regrow hair on the top of the scalp .

Warnings

· For external use only.
· Keep away from fire and flame.

Do not use if
·you have no family history of hair loss. Hair loss is sudden and/or patchy.
·you do not know the reason for your hair loss.
·you are under 18 years of age.Do not use it on babies and children.
·the scalp is red, inflamed, infected, irritated, or painful.
·you are using other medicines on your scalp.

When Using

When Using this product:
■ Do not apply on other parts of the body.
■ Avoid contact with eyes. In case of accidental contact, rinse eyes with a large amount of cool tap water.
■ lt takes time to regrow hair.
You may need to use this product once a day for at least 4 months before you see results.

Stop Use

Ask a doctor before use if you have HEART DISEASE. Stop Using and ask a doctor if
· chest pain, rapid heart beat, faintness, or dizziness occurs.
· sudden, unexplained weight gain occurs.
· your hands or feet swell.
· scalp irritation or redness occurs.
· you get unwanted facial hair growth.
· you do not see hair regrowth in 4 months.

Ask Doctor

Ask a doctor before use if you have HEART DISEASE. Stop Using and ask a doctor if
· chest pain, rapid heart beat, faintness, or dizziness occurs.
· sudden, unexplained weight gain occurs.
· your hands or feet swell.
· scalp irritation or redness occurs.
· you get unwanted facial hair growth.
· you do not see hair regrowth in 4 months.

Keep out of reach of Children. In case of accidental ingestion, get medical help or contact a poison control center immediately.

Directions

.Wash the scalp before use .
.Apply 2-3 pumps once daily to the affected scalp, then gently massage it in. For best results, leave the product on for at least 4 hours before washing hair .

Other information

· If you are using other drugs, please consult your physician or pharmacist before using this product.
· Store in a dry place at 20~25°C (68~77°F).

Inactive ingredients

PROPYLENE GLYCOL
WATER
Polysorbate 20
POLYSORBATE 20
DIMETHYL ISOSORBIDE
HYDROLYZED RHODOPHYCEAE EXTRACT
1,2-Hexanediol
Biotin
Caffeine
Rosmarinus Officinalis (Rosemary) Extract
Panax Ginseng Root Extract
Simmondsia Chinensis (Jojoba) Seed Oil
Platycladus Orientalis Leaf Extract
Glyceryl Caprylate
Hydroxyacetophenone
Ethylhexylglycerin